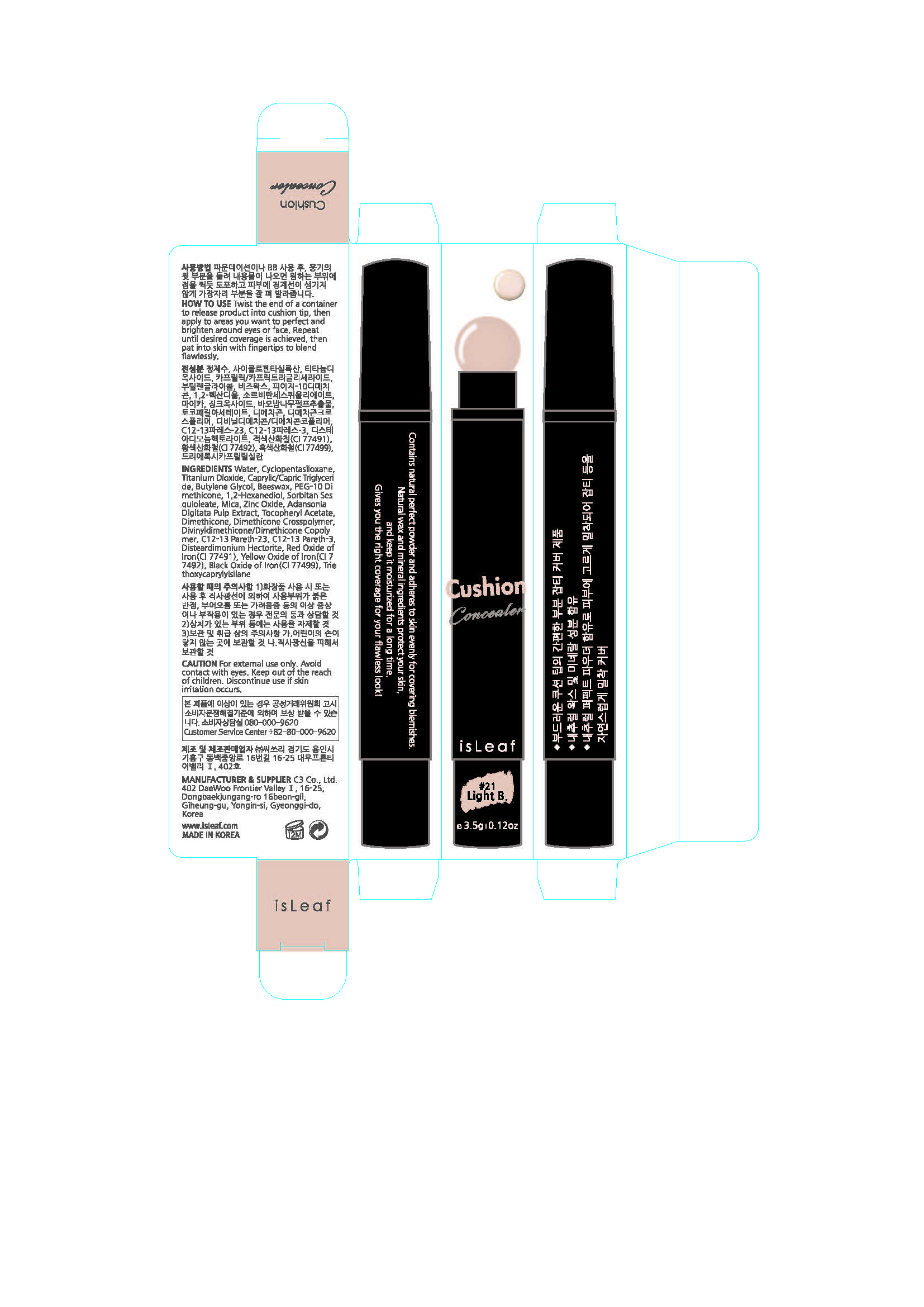 DRUG LABEL: isLeaf Cushion Concealer 23
NDC: 70818-002 | Form: LIQUID
Manufacturer: C3 Co., Ltd.
Category: otc | Type: HUMAN OTC DRUG LABEL
Date: 20170807

ACTIVE INGREDIENTS: ZINC OXIDE 1.6 g/100 g
INACTIVE INGREDIENTS: WATER; ALLANTOIN; HYALURONATE SODIUM

Drug Facts

ACTIVE INGREDIENT

titanium dioxide

INACTIVE INGREDIENT

wter butylene glycol, beeswas, etc.

PURPOSE

brighten around eyes or face

keep out of reach of the children

INDICATIONS AND USAGE

Click end to release product into brush, then apply to areas you want to perfect and brighten around eyes or face. Repeat until desired coverage is achieved, then pat into skin with fingertips to blend flawlessly.

WARNINGS

1. If the following symptoms occur after product use, stop using the product immediately and consult a dermatologist (continuous use can exacerbate the symptoms).
1) Occurrence of red spots, swelling, itchiness, and other skin irritation
2) If the symptoms above occur after the application area is exposed to direct sunlight
2. Do not use on open wounds, eczema, and other skin irritations
3. Precaution for Storage and Handling
1) Close the lid after use
2) Keep out of reach of infants and children
3) Do not to store in a place with high/low temperature and exposed to direct sunlight

4. Use as avoiding eye areas.

DOSAGE AND ADMINISTRATION

for external use only